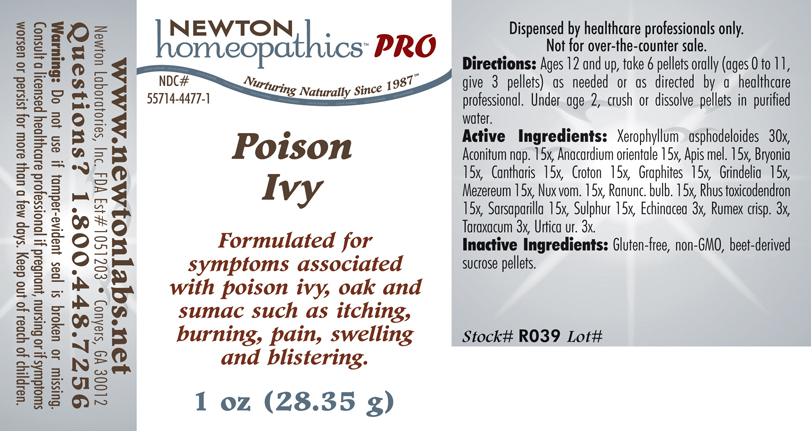 DRUG LABEL: Poison Ivy 
NDC: 55714-4477 | Form: PELLET
Manufacturer: Newton Laboratories, Inc.
Category: homeopathic | Type: HUMAN PRESCRIPTION DRUG LABEL
Date: 20110601

ACTIVE INGREDIENTS: Xerophyllum Asphodeloides 30 [hp_X]/1 g; Aconitum Napellus 15 [hp_X]/1 g; Anacardium Occidentale Fruit 15 [hp_X]/1 g; Apis Mellifera 15 [hp_X]/1 g; Bryonia Alba Root 15 [hp_X]/1 g; Lytta Vesicatoria 15 [hp_X]/1 g; Croton Tiglium Seed 15 [hp_X]/1 g; Graphite 15 [hp_X]/1 g; Grindelia Hirsutula Flowering Top 15 [hp_X]/1 g; Daphne Mezereum Bark 15 [hp_X]/1 g; Strychnos Nux-vomica Seed 15 [hp_X]/1 g; Ranunculus Bulbosus 15 [hp_X]/1 g; Toxicodendron Pubescens Leaf 15 [hp_X]/1 g; Smilax Regelii Root 15 [hp_X]/1 g; Echinacea, Unspecified 3 [hp_X]/1 g; Rumex Crispus Root 3 [hp_X]/1 g; Taraxacum Officinale 3 [hp_X]/1 g; Urtica Urens 3 [hp_X]/1 g; Sulfur 15 [hp_X]/1 g
INACTIVE INGREDIENTS: Sucrose

Poison Ivy

INDICATIONS & USAGE SECTION

Poison Ivy Formulated for symptoms associated with poison ivy, oak and sumac such as itching, burning, pain, swelling and blistering.

DOSAGE & ADMINISTRATION SECTION

Directions: Ages 12 and up, take 6 pellets orally (ages 0 to 11, give 3 pellets) as needed or as directed by a healthcare professional. Under age 2, crush or dissolve pellets in purified water.

ACTIVE INGREDIENT SECTION

Xerophyllum asphodeloides 30x, Aconitum nap. 15x, Anacardium occidentale 15x, Apis mel. 15x, Bryonia 15x, Cantharis 15x, Croton 15x, Graphites 15x, Grindelia 15x, Mezereum 15x, Nux vom. 15x, Ranunc. bulb. 15x, Rhus toxicodendron 15x, Sarsaparilla 15x, Sulphur 15x, Echinacea 3x, Rumex crisp. 3x, Taraxacum 3x, Urtica ur. 3x.

PURPOSE SECTION

Formulated for symptoms associated with poison ivy, oak and sumac such as itching, burning, pain, swelling and blistering.

INACTIVE INGREDIENT SECTION

Gluten-free, non-GMO, beet-derived sucrose pellets.

QUESTIONS? SECTION

www.newtonlabs.net Newton Laboratories, Inc. FDA Est # 1051203 - Conyers, GA 30012
Questions? 1.800.448.7256

WARNINGS SECTION

Warning: Do not use if tamper - evident seal is broken or missing. Consult a licensed healthcare professional if pregnant, nursing or if symptoms worsen or persist for more than a few days. Keep out of reach of children.

PREGNANCY OR BREAST FEEDING SECTION

Consult a licensed healthcare professional if pregnant, nursing or if symptoms worsen or persist for more than a few days.

KEEP OUT OF REACH OF CHILDREN SECTION

Keep out of reach of children.